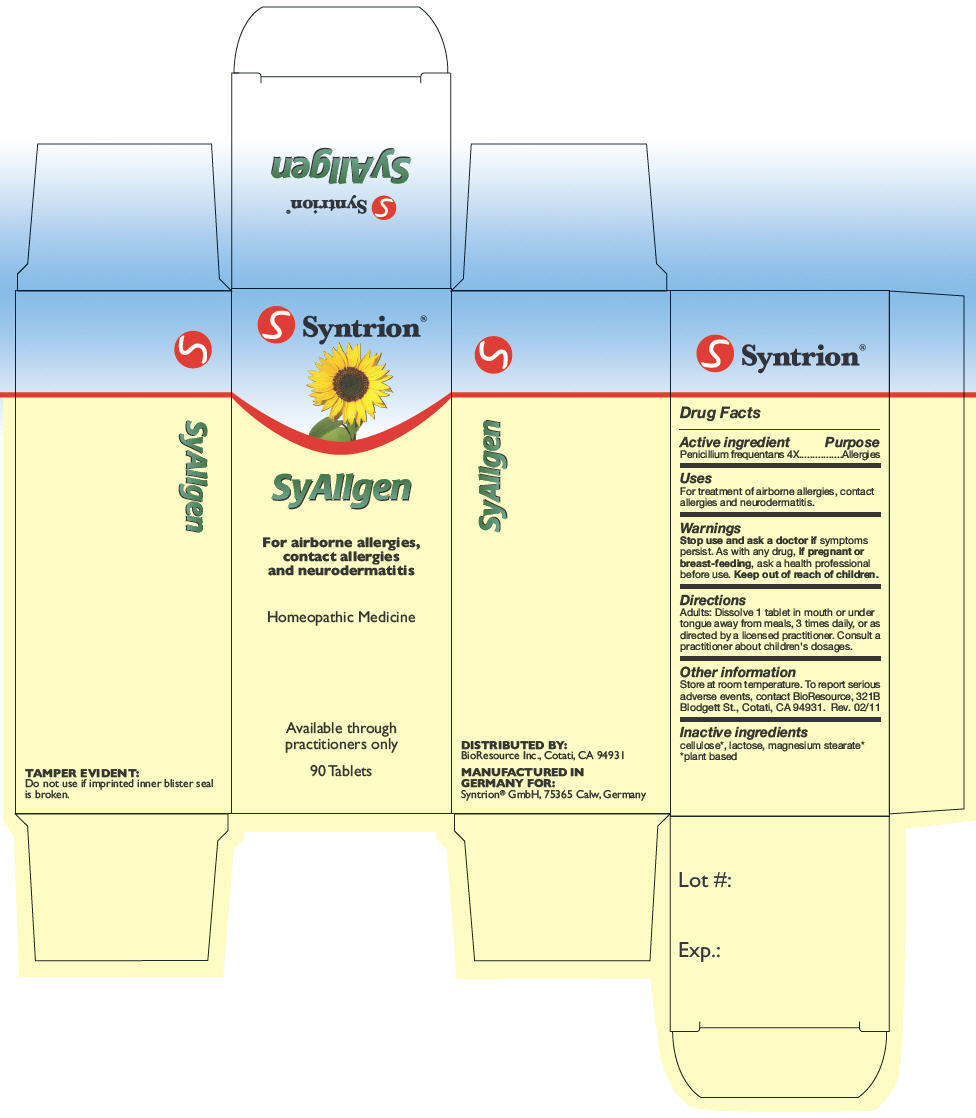 DRUG LABEL: SyAllgen
NDC: 10424-156 | Form: TABLET
Manufacturer: Syntrion GmbH
Category: homeopathic | Type: HUMAN OTC DRUG LABEL
Date: 20110707

ACTIVE INGREDIENTS: Penicillium Glabrum 4 [hp_X]/1 1
INACTIVE INGREDIENTS: powdered cellulose; lactose; magnesium stearate

SyAllgen

Drug Facts

Active ingredient

Penicillium frequentans 4X

Purpose

Allergies

Uses

For treatment of airborne allergies, contact allergies and neurodermatitis.

Warnings

Stop use and ask a doctor if symptoms persist.

PREGNANCY OR BREAST FEEDING

As with any drug, if pregnant or breast-feeding, ask a health professional before use.

Keep out of reach of children.

Directions

Adults

Dissolve 1 tablet in mouth or under tongue away from meals, 3 times daily, or as directed by a licensed practitioner. Consult a practitioner about children's dosages.

Other information

Store at room temperature. To report serious adverse events, contact BioResource, 321B Blodgett St., Cotati, CA 94931. Rev. 02/11

Inactive ingredients

cellulose [plant based] , lactose, magnesium stearate

DISTRIBUTED BY:
BioResource Inc., Cotati, CA 94931

MANUFACTURED IN GERMANY FOR:
Syntrion® GmbH, 75365 Calw, Germany

PRINCIPAL DISPLAY PANEL - 90 Tablet Carton

S Syntrion®

SyAllgen

For airborne allergies,
contact allergies
and neurodermatitis

Homeopathic Medicine

Available through
practitioners only

90 Tablets